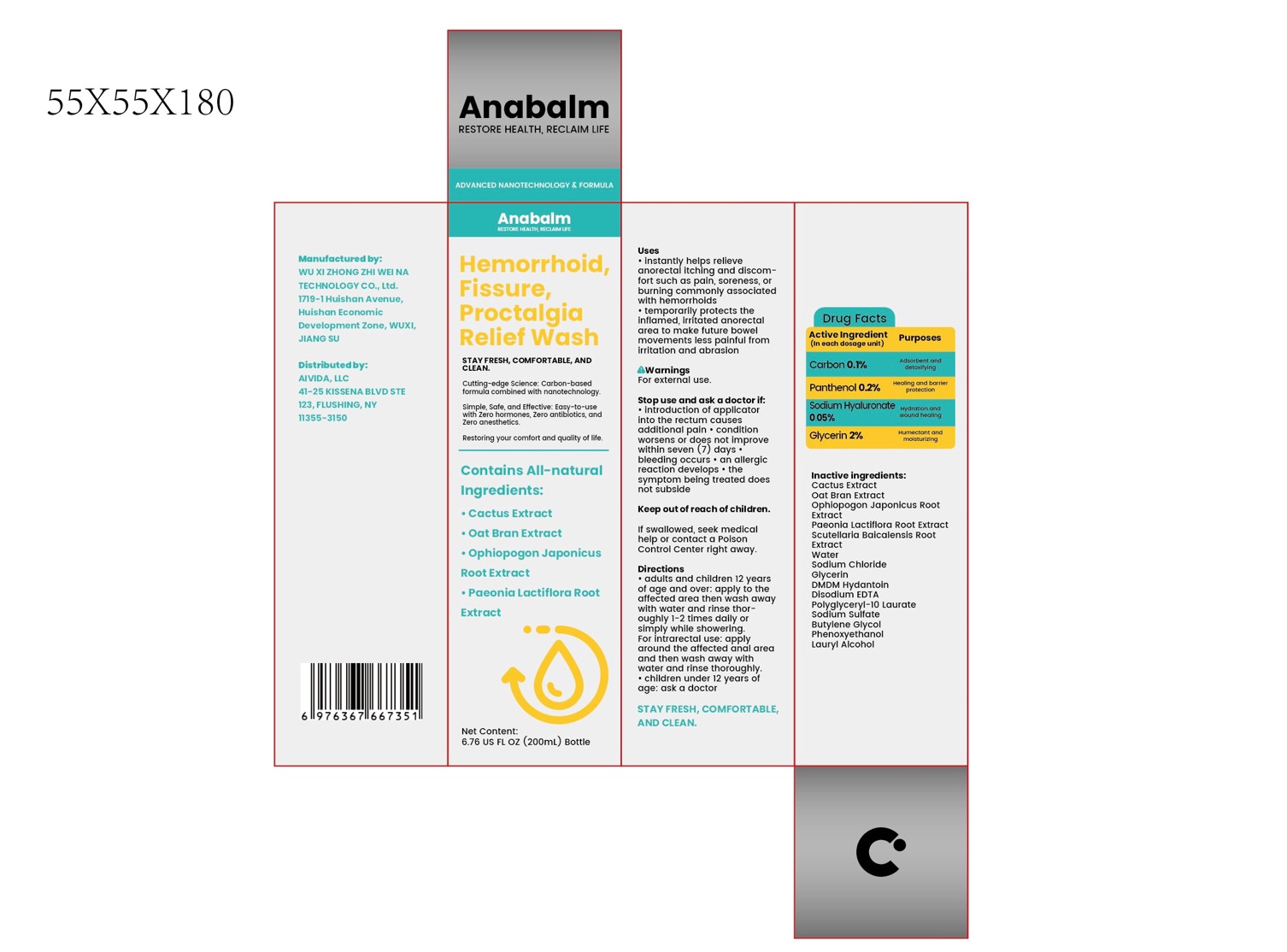 DRUG LABEL: Hemorrhoid, Fissure, Proctalgia Relief Wash
NDC: 84533-002 | Form: LIQUID
Manufacturer: WU XI ZHONG ZHI WEI NA TECHNOLOGY CO., Ltd.
Category: otc | Type: HUMAN OTC DRUG LABEL
Date: 20260114

ACTIVE INGREDIENTS: GLYCERIN 2 g/100 mL; HYALURONATE SODIUM 0.05 g/100 mL; PANTHENOL 0.2 g/100 mL; ACTIVATED CHARCOAL 0.1 g/100 mL
INACTIVE INGREDIENTS: DMDM HYDANTOIN; PAEONIA LACTIFLORA ROOT; LAURYL ALCOHOL; SODIUM CHLORIDE; POLYGLYCERYL-10 LAURATE; EDETATE DISODIUM; SCUTELLARIA BAICALENSIS ROOT; PHENOXYETHANOL; WATER; OAT BRAN; OPUNTIA FICUS-INDICA; SODIUM SULFATE; BUTYLENE GLYCOL; OPHIOPOGON JAPONICUS ROOT

84533-002 Hemorrhoid, Fissure, Proctalgia Relief Wash

ACTIVE INGREDIENT

Carbon 0.1%
Panthenol 0.2%
Sodium Hyaluronate 0.05%
Glycerin 2%

PURPOSE

Adsorbent and detoxifying
Healing and barrier protection
Hydration and wound healing
Humectant and moisturizing

KEEP OUT OF REACH OF CHILDREN

If swallowed, seek medicalhelp or contact a PoisonControl Center right away.

INDICATIONS AND USAGE

instantly helps relieveanorectal itching and discom-fort such as pain, soreness, orburning commonly associatedwith hemorrhoids
temporarily protects theinflamed, irritated anorectalarea to make future bowelmovements less painful fromirritation and abrasion

WARNINGS

For external use.

DOSAGE AND ADMINISTRATION

adults and children 12 yearsof age and over: apply to theaffected area then wash awaywith water and rinse thor-oughly 1-2 times dally orsimply while showering.For intrarectal use: applyaround the affected anal areaand then wash away withwater and rinse thoroughly.
children under 12 years ofage: ask a doctor

STORAGE AND HANDLING

STAY FRESH,COMFORTABLE,AND CLEAN.

INACTIVE INGREDIENT

Cactus Extract
Oat Bran Extract
Ophiopogon Japonicus Root Extract
Paeonia Lactiflora Root Extract
Scutellaria Baicalensis Root Extract
Water
Sodium Chloride
DMDM Hydantoin
Disodium EDTA
Polyglyceryl-10 Laurate
Sodium Sulfate
Butylene Glycol
Phenoxyethanol
Lauryl Alcohol